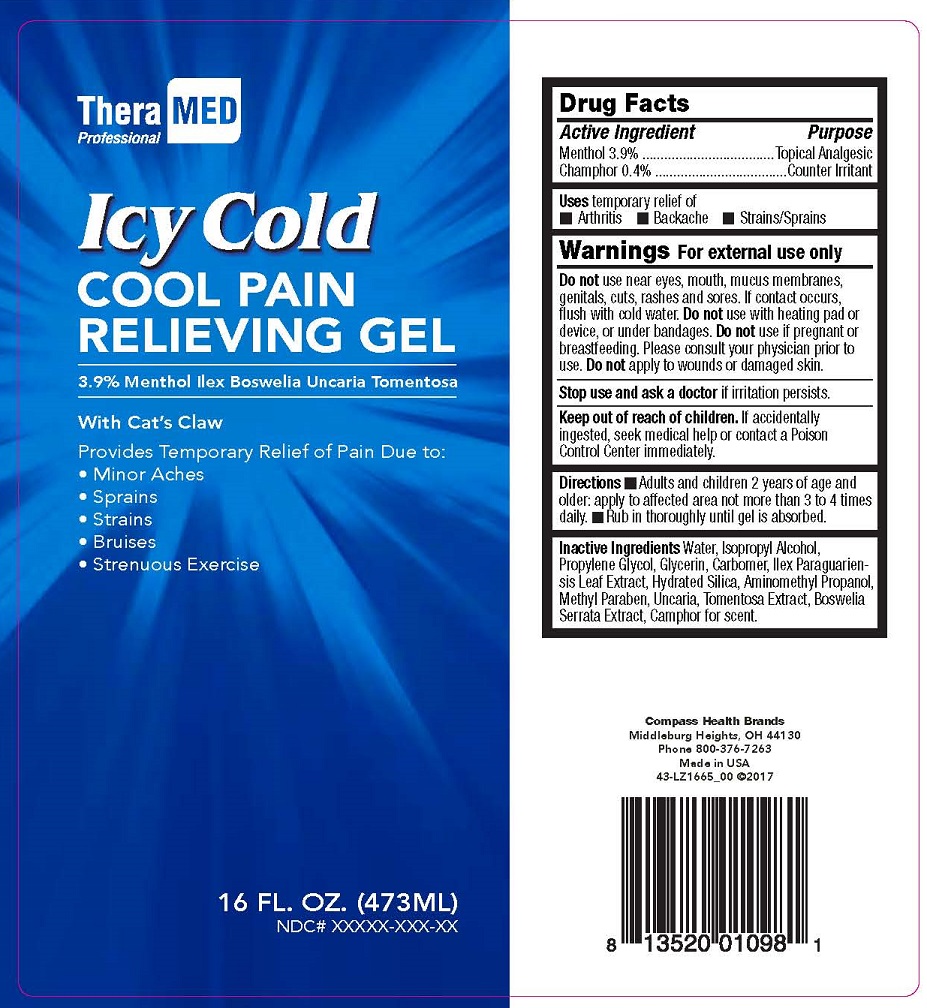 DRUG LABEL: ICY COLD COOL PAIN RELIEVING
NDC: 71323-101 | Form: GEL
Manufacturer: COMPASS HEALTH BRANDS CORP.
Category: otc | Type: HUMAN OTC DRUG LABEL
Date: 20170322

ACTIVE INGREDIENTS: MENTHOL 3.9 g/100 mL; CAMPHOR (SYNTHETIC) 0.4 g/100 mL
INACTIVE INGREDIENTS: WATER; ISOPROPYL ALCOHOL; PROPYLENE GLYCOL; GLYCERIN; CARBOMER 940; ILEX PARAGUARIENSIS LEAF; SILICON; AMINOMETHYLPROPANOL; METHYLPARABEN; UNCARIA TOMENTOSA WHOLE; BOSWELLIA SERRATA WHOLE

ACTIVE INGREDIENTS

MENTHOL 3.9%

CAMPHOR 0.4%

PURPOSE

TOPICAL ANALGESIC

COUNTER IRRITANT

USES

temporary relief of

- Arthritis
- Backache
- Strains/Sprains

WARNINGS

FOR EXTERNAL USE ONLY

Do not use near eyes, mouth, mucus membranes, genitals, cuts, rashes and sores. If contact occurs, flush with cold water. Do not use with heating pad or device, or under bandages. Do not use if pregnant or breastfeeding. Please consult your physician prior to use. Do not apply to wounds or damaged skin.

Stop use and ask a doctor if irritation persists.

Keep out of reach of children. If accidentally ingested, seek medical help or contact a Poison Control Center immediately.

DIRECTIONS

- Adults and children 2 years of age and older: apply to affected area not more than 3 to 4 times daily.
- Rub in thoroughly until gel is absorbed.

INACTIVE INGREDIENTS

Water, Isopropyl Alcohol, Propylene Glycol, Glycerin, Carbomer, Ilex Paraguariensis Leaf Extract, Hydrated Silica, Aminomethyl Propanol, Methyl Paraben, Uncaria Tomentosa Extract, Boswelia Serrata Extract, Camphor for scent.